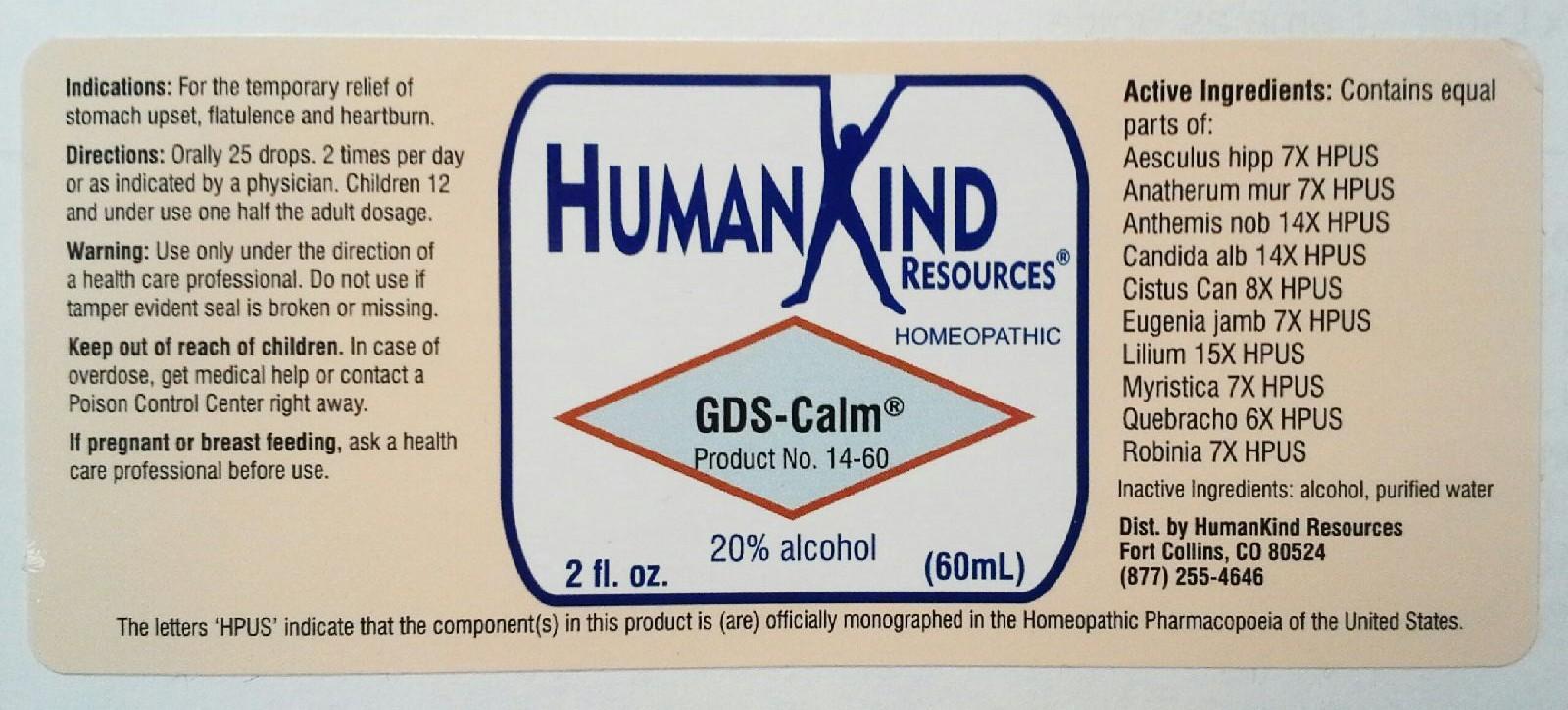 DRUG LABEL: GDS-Calm
NDC: 64616-092 | Form: LIQUID
Manufacturer: Vitality Works, Inc.
Category: homeopathic | Type: HUMAN OTC DRUG LABEL
Date: 20251217

ACTIVE INGREDIENTS: HORSE CHESTNUT 7 [hp_X]/1 mL; CHRYSOPOGON ZIZANIOIDES ROOT 7 [hp_X]/1 mL; CHAMAEMELUM NOBILE 14 [hp_X]/1 mL; CANDIDA ALBICANS 14 [hp_X]/1 mL; HELIANTHEMUM CANADENSE 8 [hp_X]/1 mL; SYZYGIUM JAMBOS SEED 7 [hp_X]/1 mL; LILIUM LANCIFOLIUM WHOLE FLOWERING 15 [hp_X]/1 mL; VIROLA SEBIFERA RESIN 7 [hp_X]/1 mL; ASPIDOSPERMA QUEBRACHO-BLANCO BARK 6 [hp_X]/1 mL; ROBINIA PSEUDOACACIA BARK 7 [hp_X]/1 mL
INACTIVE INGREDIENTS: ALCOHOL; WATER

GDS-Calm

GDS-Calm

Aesculus Hippocastanum 7X Eugenia Jambosa 7X

Anatherum Muricatum 7X Lilium Tigrinum 15X

Anthemis Nobilis 14X Myristica Sebifera 7X

Candida Albicans 14X Quebracho 6X

Cistus Canadensis 8X Robinia Pseudoacacia 7X

GDS-Calm

Alcohol, Purified Water

GDS-Calm

Use only under the direction of a health care professional. Do not use if tamper evident seal is broken or missingl.

GDS-Calm

Keep out of reach of children. In case of overdose, get medical help or contact a Poison Control Center right away.

GDS-Calm

For the temporary relief of stomach upset, flatulence and heartburn.

GDS-Calm

Orally 25 drops, 2 times per day or as indicated by a physician. Children 12 and under use one half the adult dosage.

GDS-Calm

Digestive tract calming.